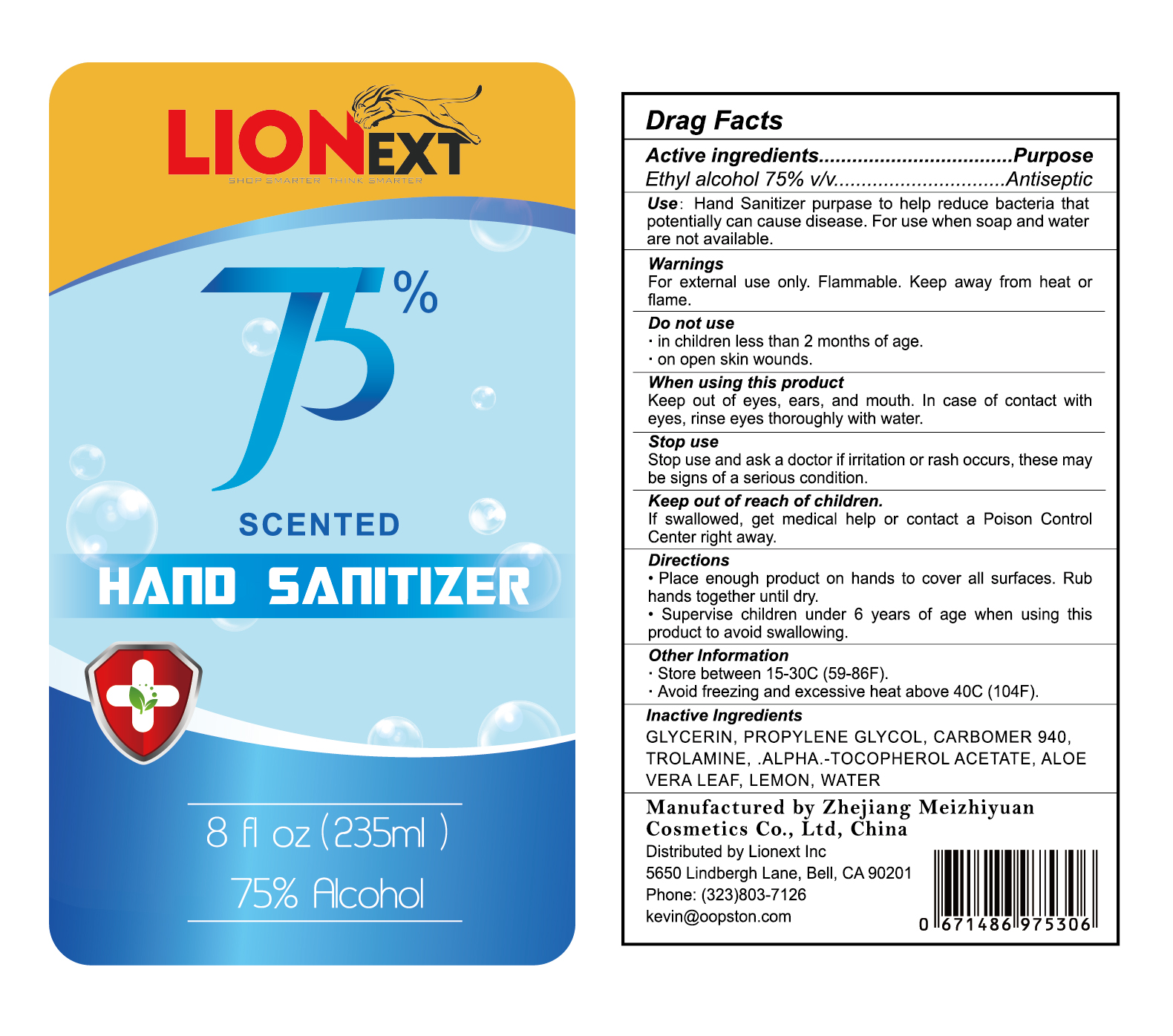 DRUG LABEL: Lionext Hand Sanitizer
NDC: 54304-842 | Form: LIQUID
Manufacturer: Zhejiang Meizhiyuan Cosmetics Co., Ltd
Category: otc | Type: HUMAN OTC DRUG LABEL
Date: 20200609

ACTIVE INGREDIENTS: ALCOHOL 75 mL/100 mL
INACTIVE INGREDIENTS: GLYCERIN; PROPYLENE GLYCOL; CARBOMER 940; TROLAMINE; .ALPHA.-TOCOPHEROL ACETATE; ALOE VERA LEAF; LEMON; WATER

Zhejiang Meizhiyuan Cosmetics Co., Ltd

Active Ingredient

Ethyl Alcohol 75% v/v

Purpose

Ethyl Alcohol Antiseptic

Use

Hand Sanitizer to help reduce bacteria that potentially can cause disease. For use when soap and water are not available.

Warnings

For external use only. Flammable. Keep away from heat or flame.

Do not use

- in children less than 2 months of age.
- on open skin wounds.

When using this product

Keep out of eyes, ears, and mouth. In case of contact with eyes, rinse eyes thoroughly with water.

Stop use

Stop use and ask a doctor if irritation or rash occurs. These may be signs of a serious condition.

Keep out of reach of children.

If swallowed, get medical help or contact a Poison Control Center right away.

Directions

- Place enough product on hands to cover all surfaces. Rub hands together until dry.
- Supervise children under 6 years of age when using this product to avoid swallowing.

Other Information

- Store between 15-30C (59-86F).
- Avoid freezing and excessive heat above 40C (104F).

Manufactured by Zhejiang Meizhiyuan Cosmetics Co., Ltd, China

Distributed by Lionext Inc
5650 Lindbergh Lane, Bell, CA 90210
Phone: (323)803-7126 kevin@oopston.com

Inactive Ingredients

GLYCERIN, PROPYLENE GLYCOL, CARBOMER 940, TROLAMINE, .ALPHA.-TOCOPHEROL ACETATE, ALOE VERA LEAF, LEMON, WATER